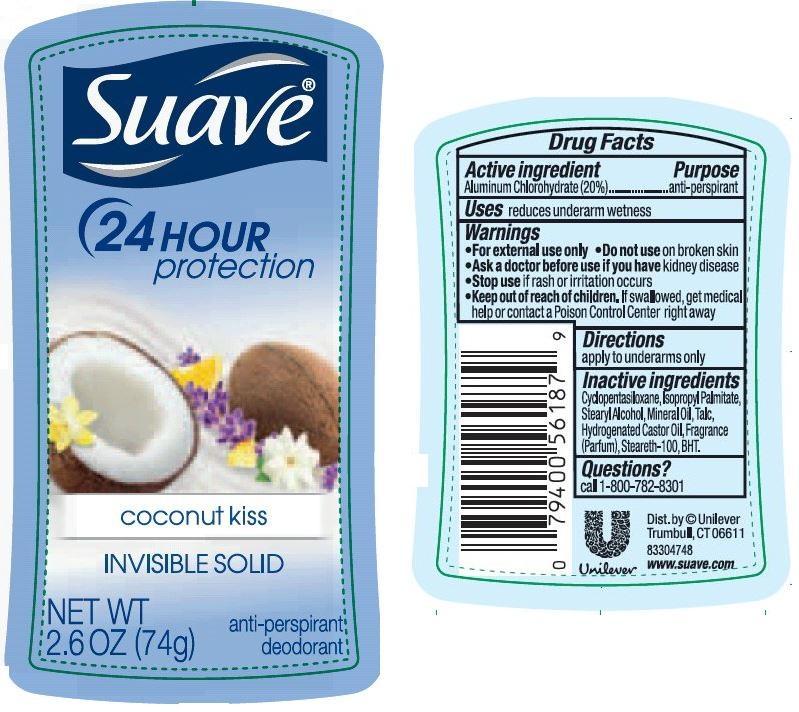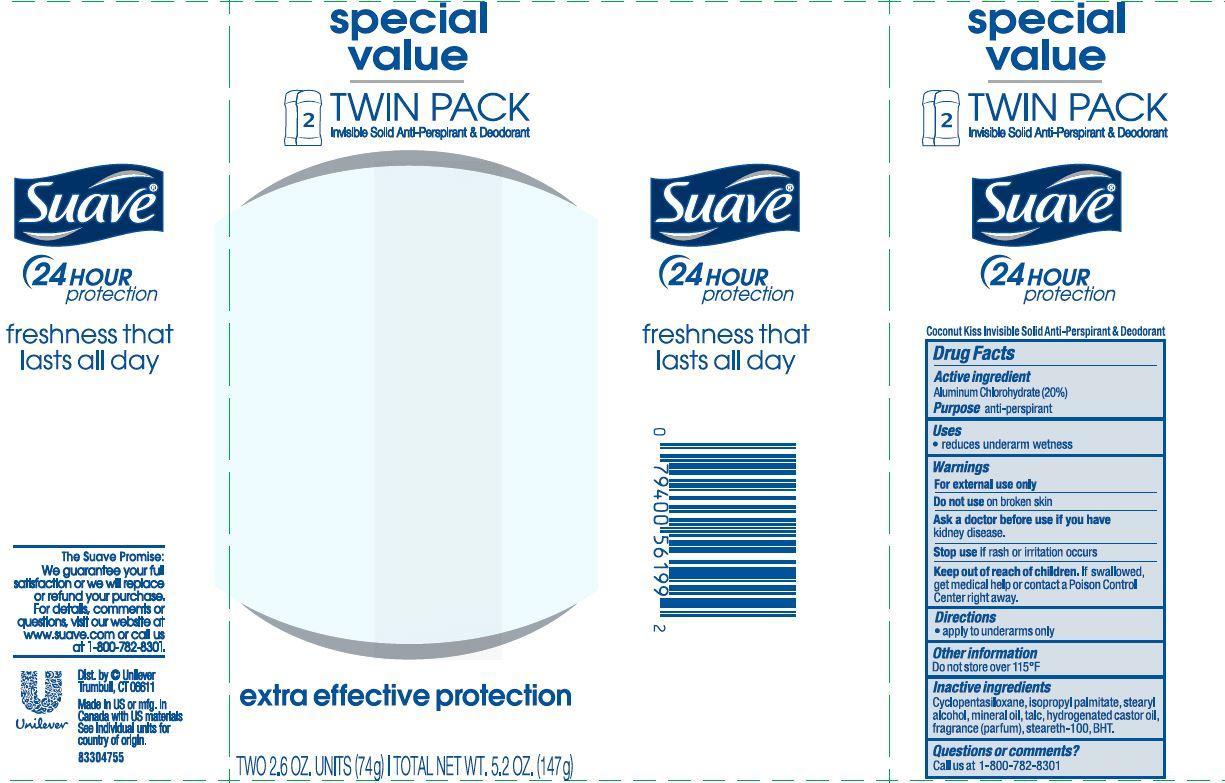 DRUG LABEL: Suave
NDC: 64942-1432 | Form: STICK
Manufacturer: Conopco Inc. d/b/a Unilever
Category: otc | Type: HUMAN OTC DRUG LABEL
Date: 20150915

ACTIVE INGREDIENTS: Aluminum Chlorohydrate 20 g/100 g
INACTIVE INGREDIENTS: CYCLOMETHICONE 5; isopropyl palmitate; STEARYL ALCOHOL; MINERAL OIL; TALC; HYDROGENATED CASTOR OIL; STEARETH-100; BUTYLATED HYDROXYTOLUENE

Suave Coconut Kiss Antiperspirant and Deodorant

Active ingredient

Aluminum Chlorohydrate (20%)

Purpose

antiperspirant

Uses

reduces underam wetness

Warnings

For external use only

Do not use on broken skin

Ask a doctor before use if you have kidney disease

Stop use if rash or irritation occurs.

Keep out of reach of children. If swallowed, get medical help or contact a Poison Control Center right away.

Directions

apply to underarms only

Inactive Ingredients
Cyclopentasiloxane, Isopropyl Palmitate, Stearyl Alcohol, Mineral Oil, Talc, Hydrogenated Castor Oil, Fragrance (Parfum), Steareth-100, BHT.

Questions?
Call 1-800-782-8301